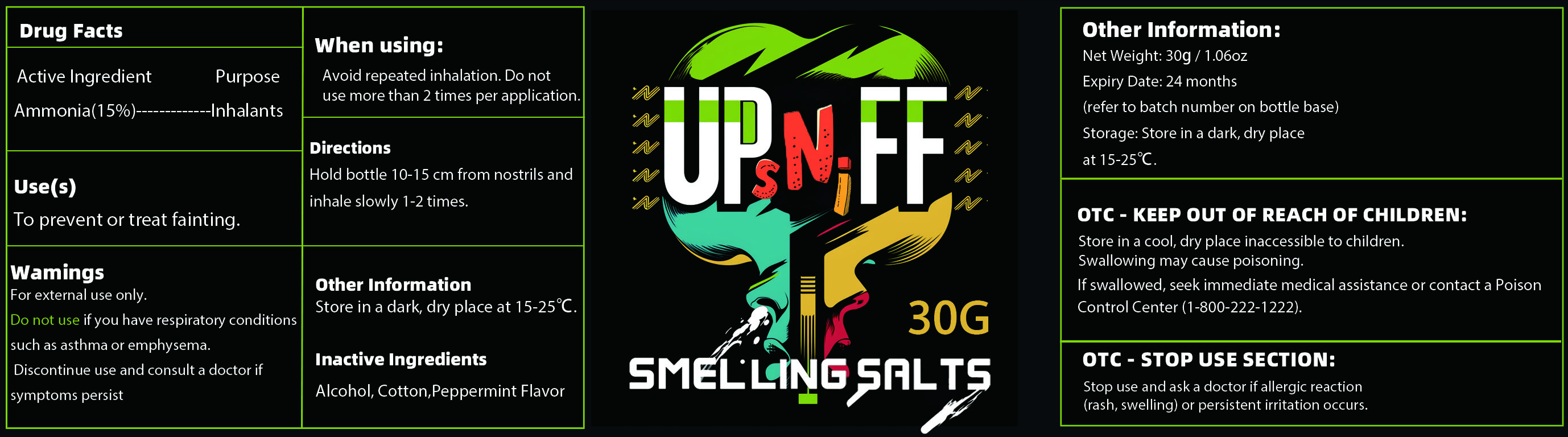 DRUG LABEL: UpSniff Smelling Salts
NDC: 85590-003 | Form: POWDER
Manufacturer: Shenzhen Nanjun Technology Co., Ltd
Category: otc | Type: HUMAN OTC DRUG LABEL
Date: 20250910

ACTIVE INGREDIENTS: AMMONIA 15 g/100 g
INACTIVE INGREDIENTS: PEPPERMINT; ALCOHOL; COTTON

85590-003

Active Ingredient

Ammonia 15%

Purpose

Inhalants

Use

To prevent or treat fainting

Warnings

For external use only.

DO NOT USE if you have respiratory conditions such as asthma or emphysema.Discontinue use and consult a doctor if symptoms persist.

When Using

Avoid repeated inhalation.Do not use more than 2 times per application.

Stop Use

Stop use and ask a doctor if allergic reaction(rash,swelling) or persistent irritation occurs.

Ask Doctor

Stop use and ask a doctor if allergic reaction(rash,swelling) or persistent irritation occurs.

Keep Out Of Reach Of Children

Store in a cool,dry place inaccessible to children. Swallowing my cause poisoning. If swallowed, seek immediate medical assistance or contact a Poison Control Center(1-800-222-1222).

Directions

Hold bottle 10-15cm from nostrils and inhale slowly 1-2 times.

Other information

Store in a dark, dry place at 15-25°C

Inactive ingredients

Alcohol,Cotton,Peppermint Flavor